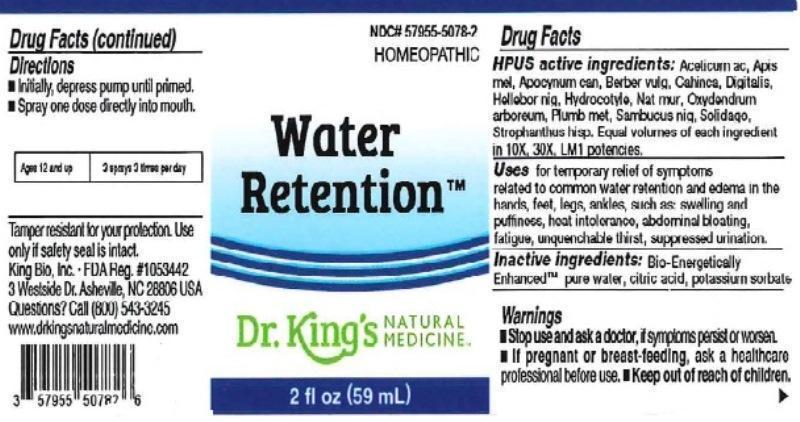 DRUG LABEL: Water Retention
NDC: 57955-5078 | Form: LIQUID
Manufacturer: King Bio Inc.
Category: homeopathic | Type: HUMAN OTC DRUG LABEL
Date: 20160622

ACTIVE INGREDIENTS: ACETIC ACID 10 [hp_X]/59 mL; APIS MELLIFERA 10 [hp_X]/59 mL; APOCYNUM CANNABINUM ROOT 10 [hp_X]/59 mL; BERBERIS VULGARIS ROOT BARK 10 [hp_X]/59 mL; CHIOCOCCA ALBA ROOT 10 [hp_X]/59 mL; DIGITALIS 10 [hp_X]/59 mL; HELLEBORUS NIGER ROOT 10 [hp_X]/59 mL; CENTELLA ASIATICA 10 [hp_X]/59 mL; SODIUM CHLORIDE 10 [hp_X]/59 mL; OXYDENDRUM ARBOREUM LEAF 10 [hp_X]/59 mL; LEAD 10 [hp_X]/59 mL; SAMBUCUS NIGRA FLOWERING TOP 10 [hp_X]/59 mL; SOLIDAGO VIRGAUREA FLOWERING TOP 10 [hp_X]/59 mL; STROPHANTHUS HISPIDUS SEED 10 [hp_X]/59 mL
INACTIVE INGREDIENTS: ANHYDROUS CITRIC ACID; POTASSIUM SORBATE; WATER

Water Retention™

ACTIVE INGREDIENT

Drug Facts__________________________________________________________________________________________________________

HPUS active ingredients: Aceticum acidum, Apis mellifica, Apocynum cannabinum, Berberis vulgaris, Cahinca, Digitalis purpurea, Helleborus niger, Hydrocotyle asiatica, Natrum muriaticum, Oxydendrum arboreum, Plumbum metallicum, Sambucus nigra, Solidago virgaurea, Strophanthus hispidus. Equal volumes of each ingredient in 10X, 30X, LM1 potencies.

INDICATIONS AND USAGE

Uses for temporary relief of symptoms related to common water retention and edema in the hands, feet, legs, ankles, such as: swelling and puffiness, heat intolerance, abdominal bloating, fatigue, unquenchable thrist, suppressed urination.

Inactive Ingredients:

Bio-Energetically Enhanced™ pure water, citric acid and potassium sorbate.

Warnings

- Stop use and ask your doctor if symptoms persist or worsen.
- If pregnant or breast-feeding, ask a healthcare professional before use.

- Keep out of reach of children.

Directions

- Initially, depress pump until primed.
- Spray one dose directly into mouth.
- Ages 12 and up: 3 sprays 3 times per day.

OTHER SAFETY INFORMATION

Tamper resistant for your protection. Use only if safety seal is intact.

PURPOSE

Uses for temporary relief of symptoms related to common water retention and edema in the hands, feet, legs, ankles, such as:

- swelling and puffiness
- heat intolerance
- abdominal bloating
- fatigue
- unquenchable thrist
- suppressed urination